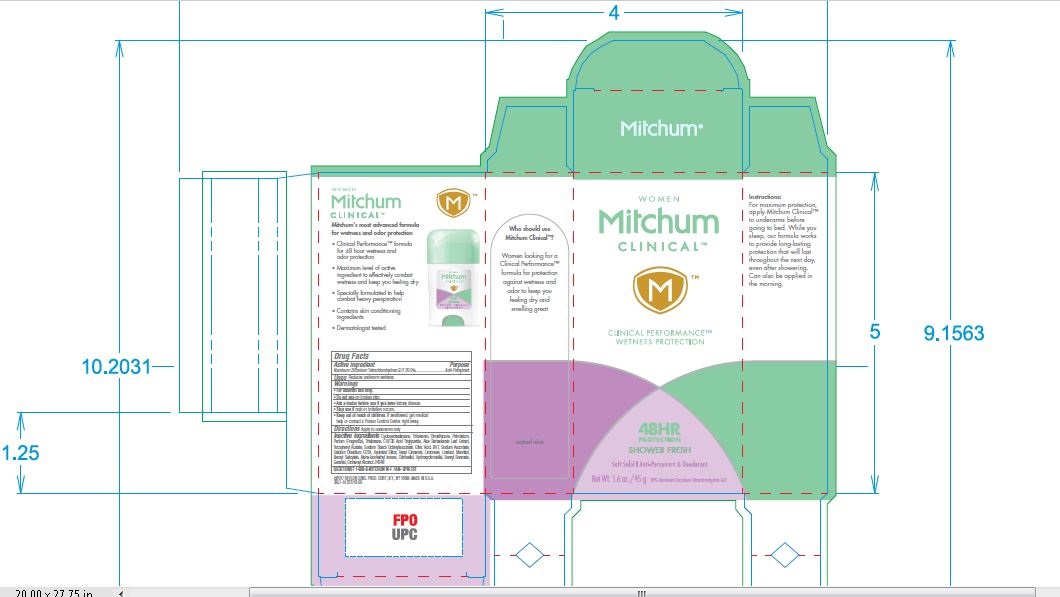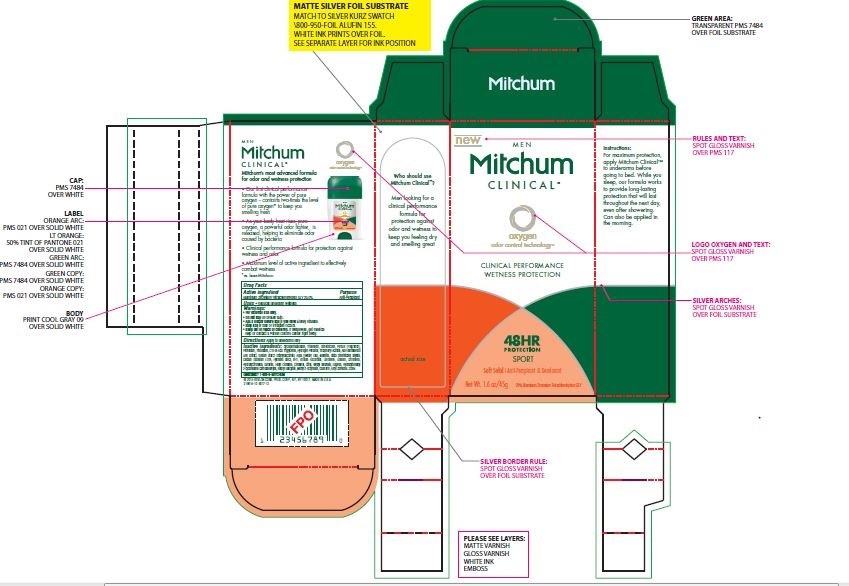 DRUG LABEL: Mitchum Clinical Soft Solid
NDC: 10967-678 | Form: STICK
Manufacturer: Revlon Consumer Products Corp.
Category: otc | Type: HUMAN OTC DRUG LABEL
Date: 20241231

ACTIVE INGREDIENTS: ALUMINUM ZIRCONIUM TETRACHLOROHYDREX GLY 0.2 g/1 g
INACTIVE INGREDIENTS: BUTYLATED HYDROXYTOLUENE; TRIBEHENIN; C18-36 ACID TRIGLYCERIDE; DIMETHICONE; PETROLATUM; ALOE VERA LEAF; ALPHA-TOCOPHEROL ACETATE; EDETATE CALCIUM DISODIUM ANHYDROUS; SODIUM STARCH GLYCOLATE TYPE A CORN; HYDRATED SILICA; MANNITOL; CYCLOPENTASILOXANE; TRISILOXANE; CITRIC ACID; SODIUM ASCORBATE

Mitchum Clinical Soft Solid - Powder Fresh

Active Ingredients

ALUMINUM ZIRCONIUM TETRACHLOROHYDREX GLY 20.0%

Keep out of reach of children

If swallowed, get medical help or call Poison Control Center right away

Inactive Ingredient section

Cyclopentasiloxane; Tribehenin; DIimethicone; Petrolatum; Parfume (Fragrance); Trisiloxane; C18-36 Acid Triglyceride; Aloe Barbadensis Leaf Extract; Tocopheryl Acetate; Sodium Starch Octenylsuccinate, Citric Acid, BHT, Sodium Ascorbate,

Calcium Disodium EDTA, Hydrated Silica, Hexyl Cinnamal, Limonene, Linalool, Mannitol,

Benzyl Salicylate, Alpha-Isomethyl Ionone, Citronellol, Hydroxycitronellal, Benzyl Benzoate,

Geraniol, Cinnamyl Alcohol.

Uses

Reducess Underarm Wetness

DOSAGE AND ADMINISTRATION

Apply to underarms only

WARNINGS

- For external use only.

• Do not use on broken skin.

• Ask a doctor before use if you have kidney disease.

• Stop use if rash or irritation occurs

INDICATIONS AND USAGE

Reduces Underarm wetness